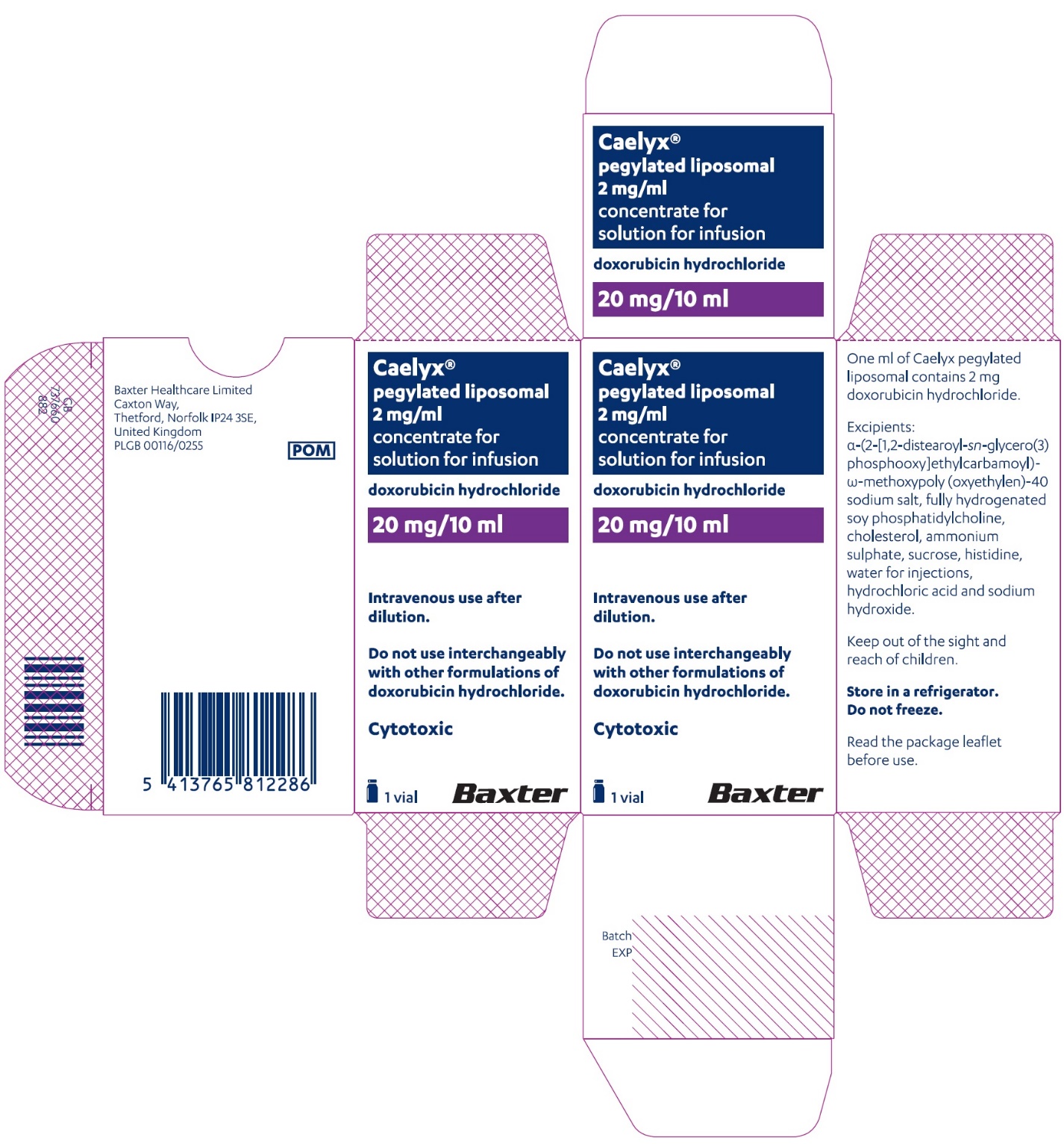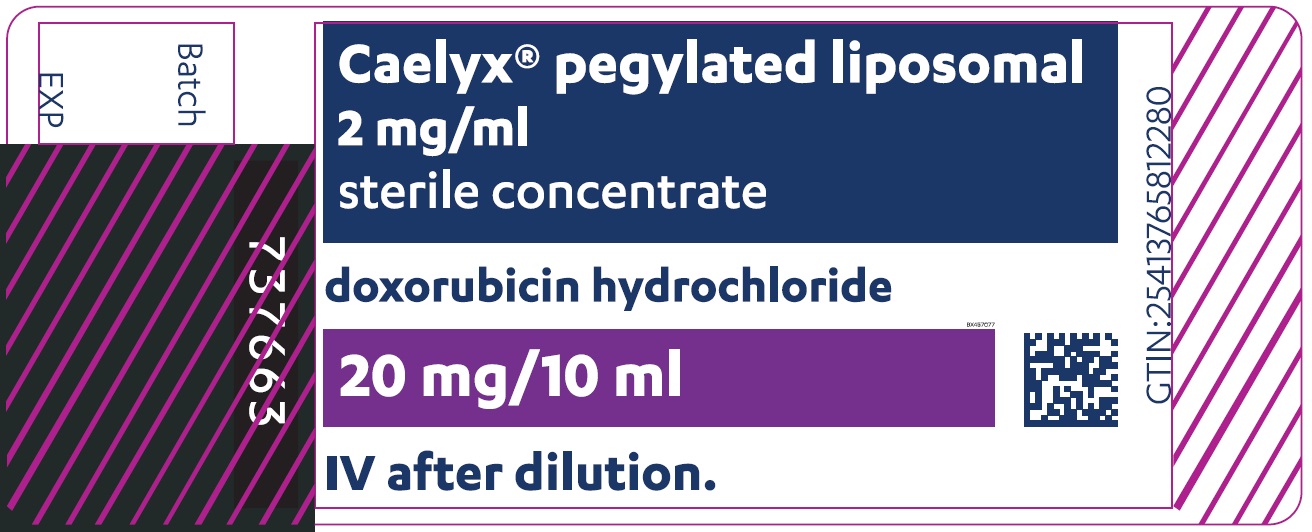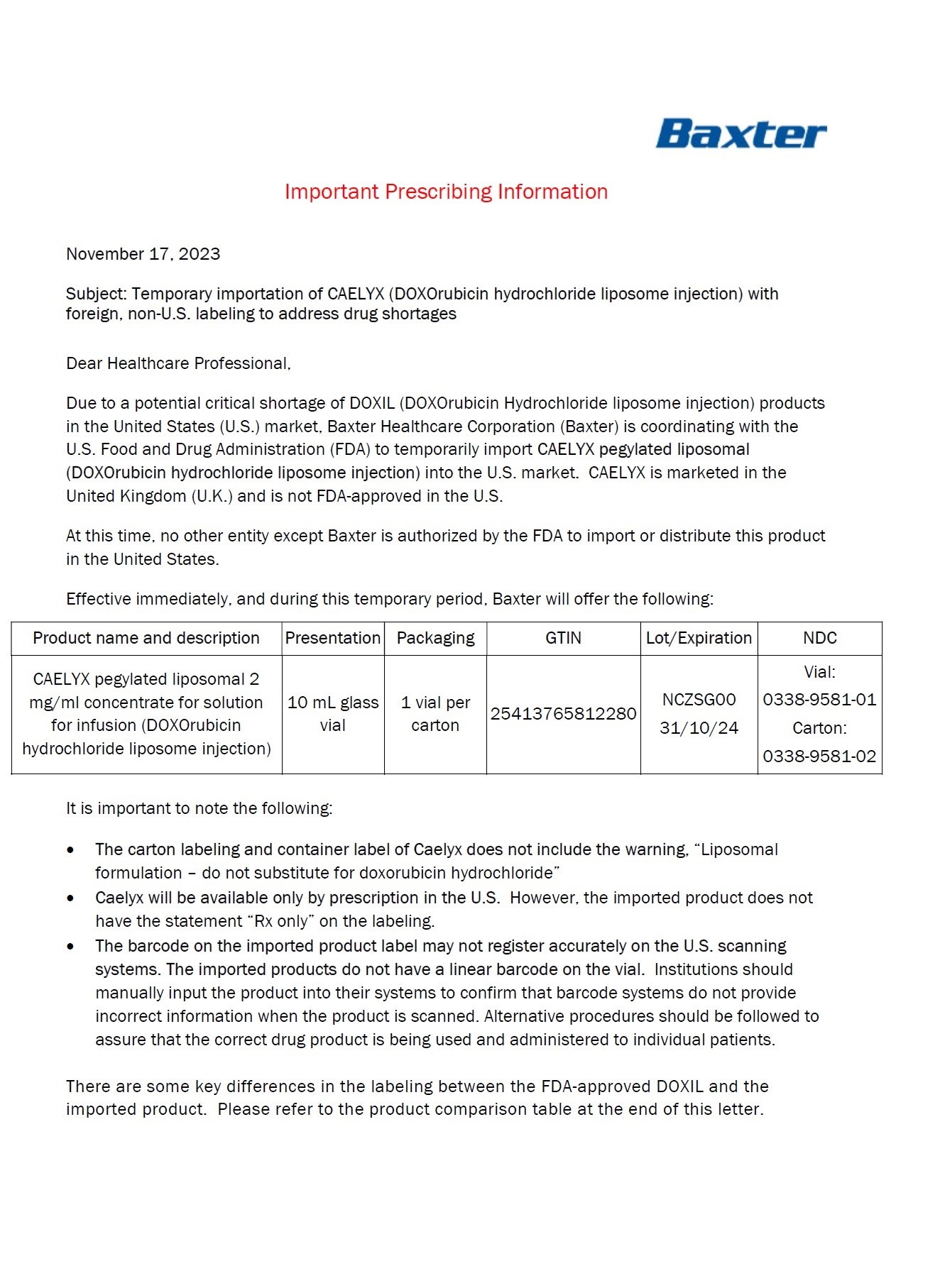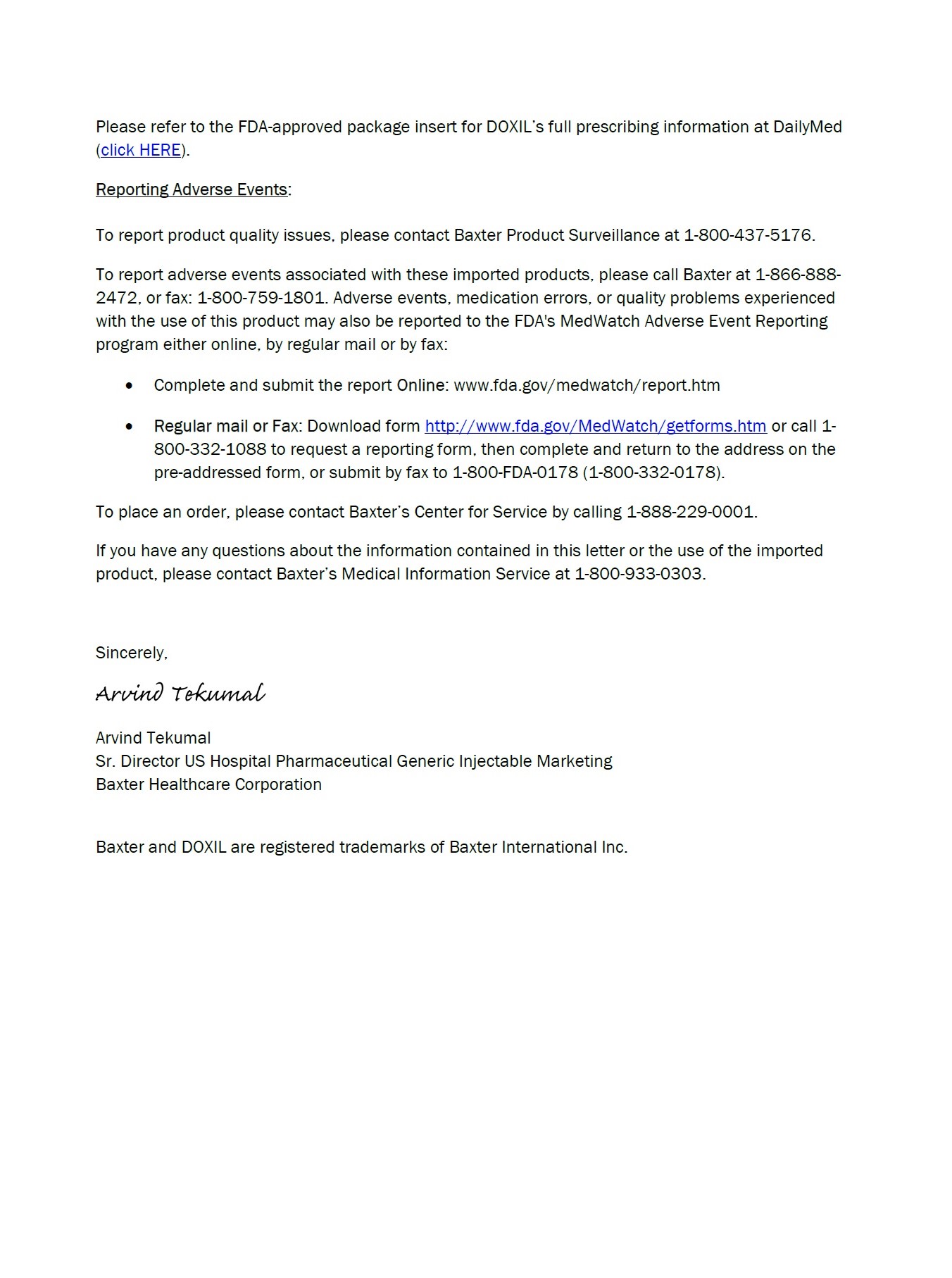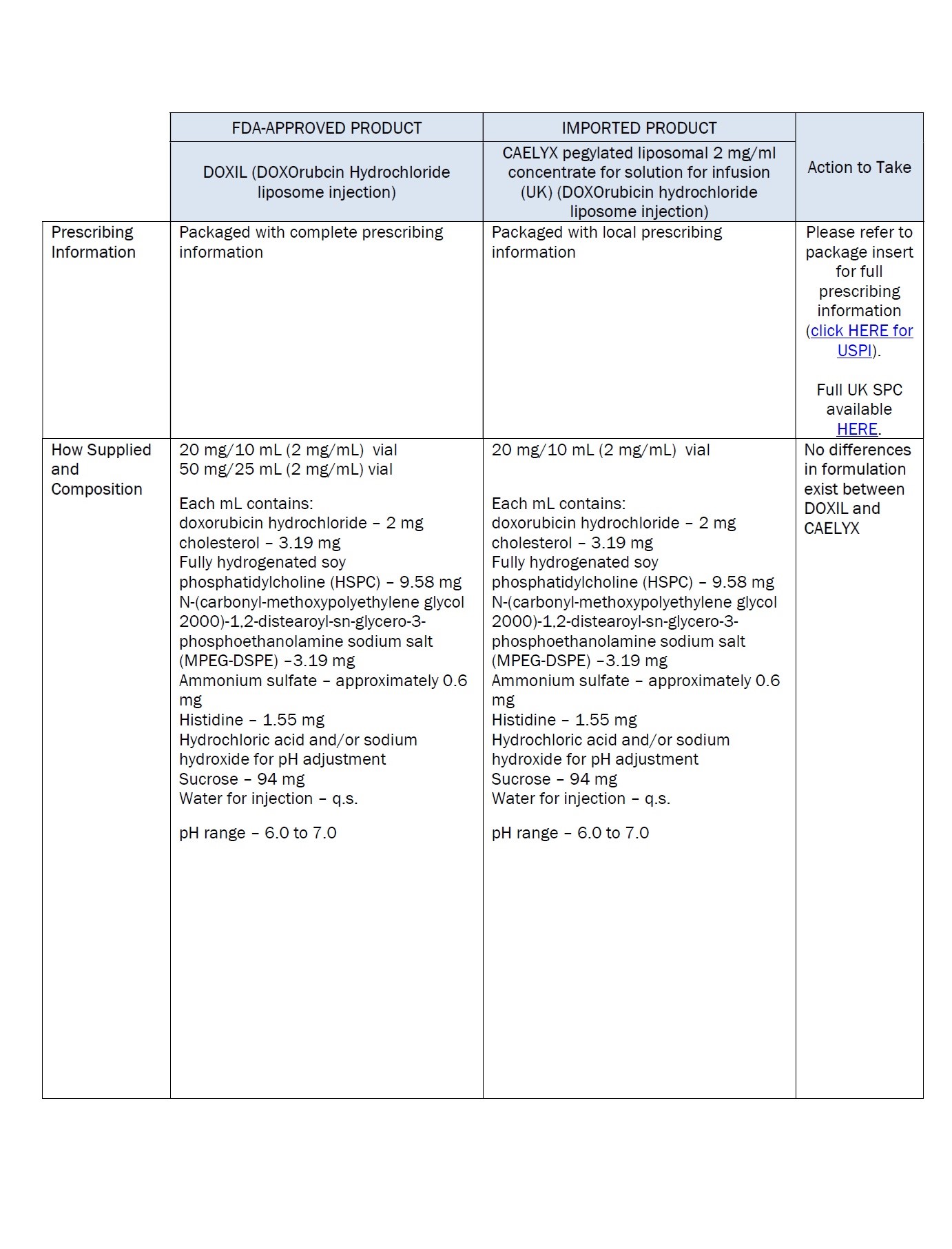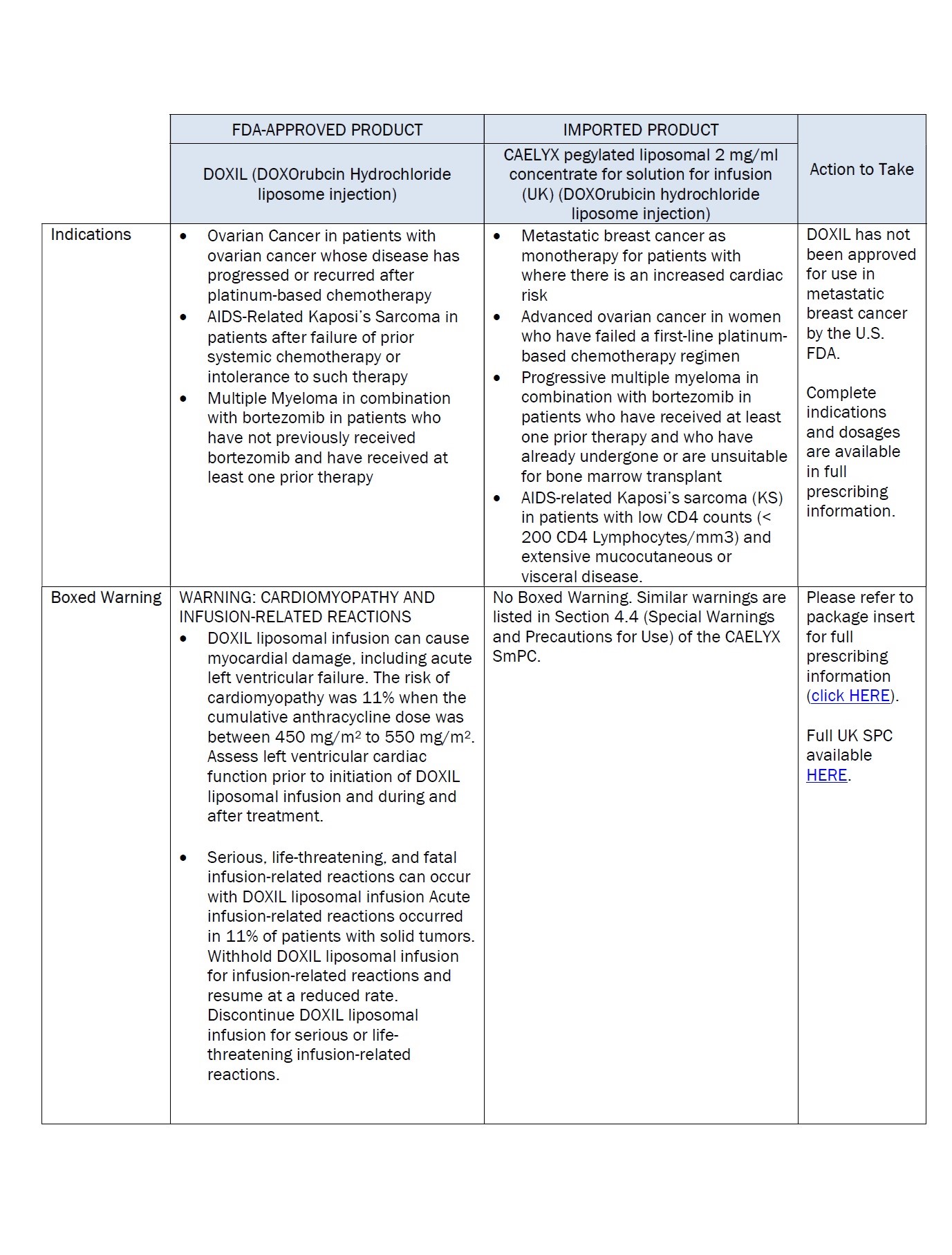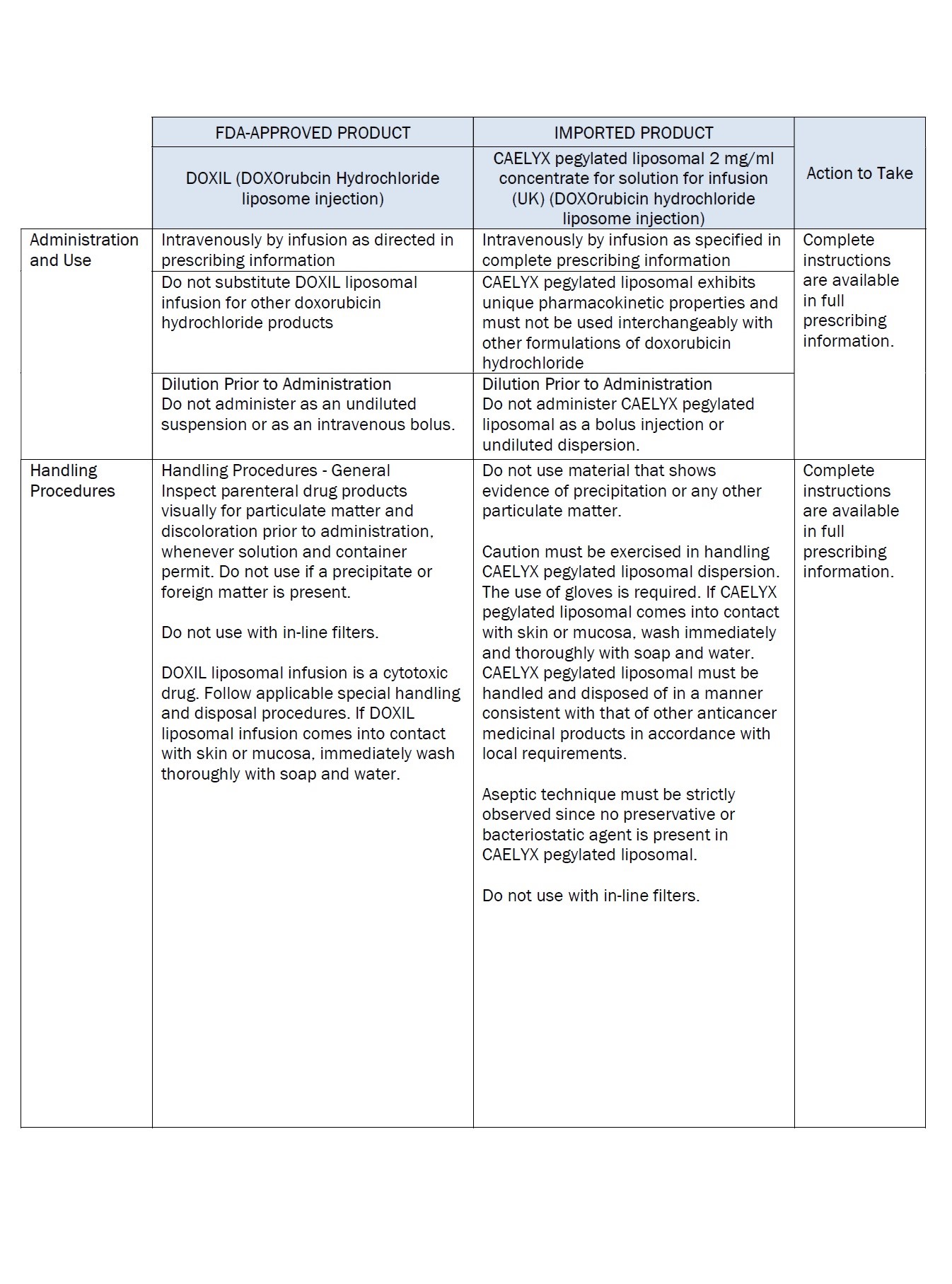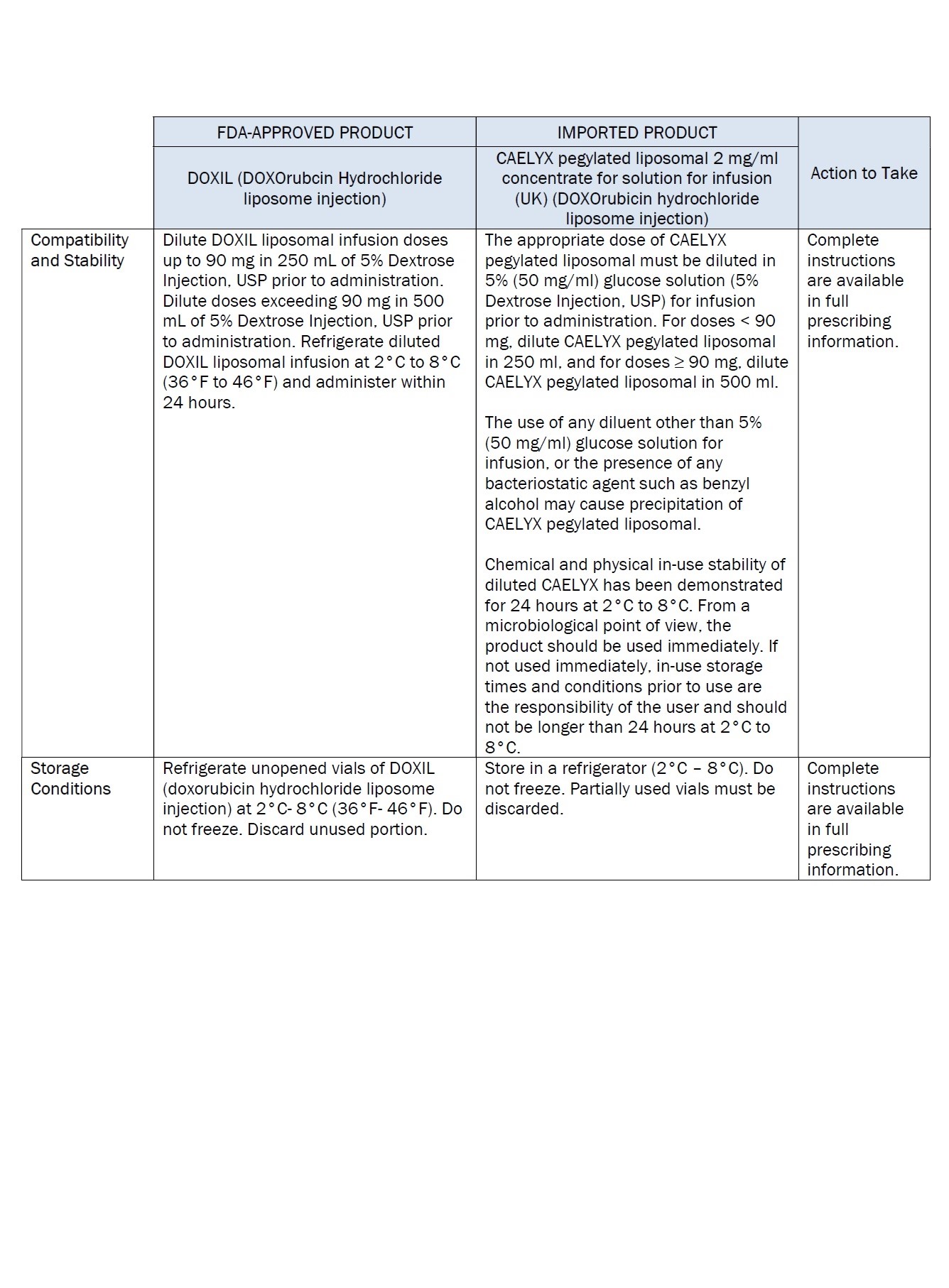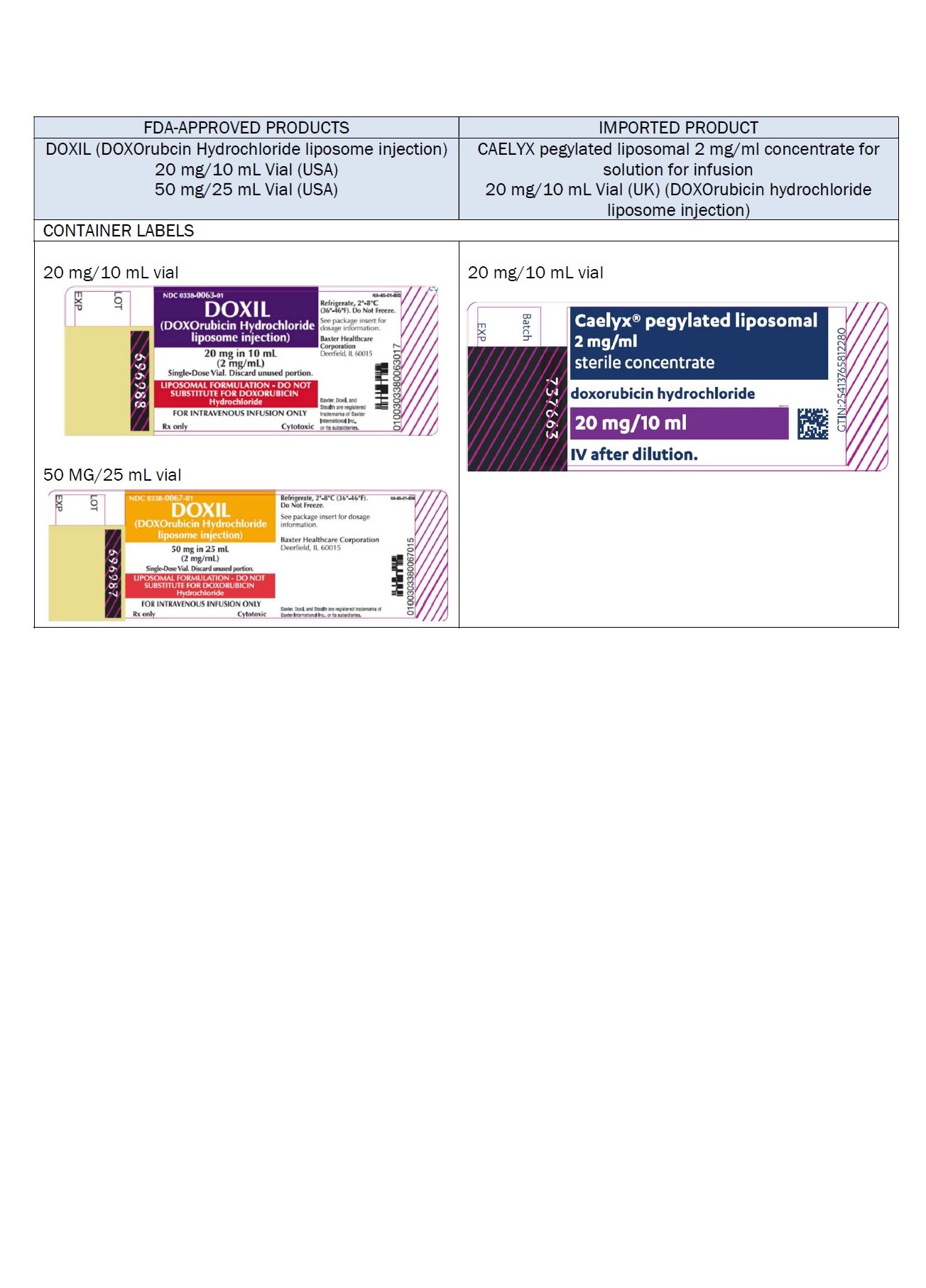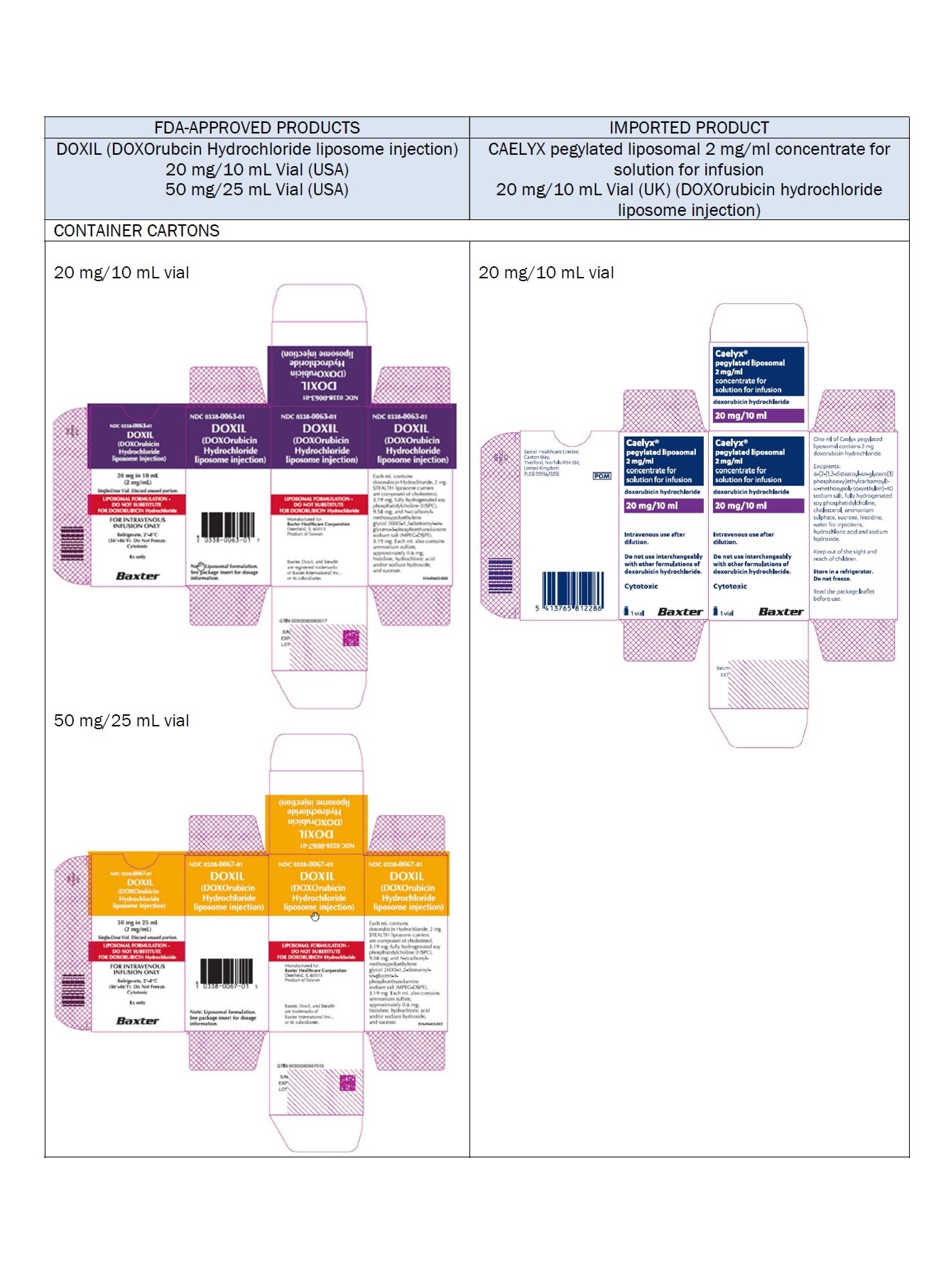 DRUG LABEL: doxorubicin hydrochloride, Liposomal
NDC: 0338-9581 | Form: INJECTION, SUSPENSION, LIPOSOMAL
Manufacturer: Baxter Healthcare Corporation
Category: prescription | Type: HUMAN PRESCRIPTION DRUG LABEL
Date: 20231219

ACTIVE INGREDIENTS: doxorubicin hydrochloride 2 mg/1 mL
INACTIVE INGREDIENTS: SODIUM N-(CARBONYL-METHOXYPOLYETHYLENE GLYCOL 2000)-1,2-DISTEAROYL-SN-GLYCERO-3-PHOSPHOETHANOLAMINE 3.19 mg/1 mL; hydrogenated soybean lecithin 9.58 mg/1 mL; cholesterol 3.19 mg/1 mL; ammonium sulfate 0.6 mg/1 mL; histidine 1.55 mg/1 mL; hydrochloric acid; sodium hydroxide; sucrose 94 mg/1 mL

Doxorubicin Hydrochloride Liposome Injection

PACKAGE/LABEL PRINCIPAL DISPLAY PANEL – 20 mg/10 mL

Caelyx® pegylated liposomal
2 mg/ml
sterile concentrate

doxorubicin hydrochloride

20 mg/10 mL

IV after dilution.

Caelyx®

pegylated liposomal

2 mg/ml

concentrate for

solution for infusion

doxorubicin hydrochloride

20 mg/10 mL

Intravenous use after

dilution.

Do not use interchangeably
with other formulations of
doxorubicin hydrochloride.

Cytotoxic

1 vial

Baxter Logo

One ml of Caelyx pegylated
liposomal contains 2 mg
doxorubicin hydrochloride.

Excipients: α-(2-[1,2-distearoyl-sn-glycero(3)
phosphooxy]ethylcarbamoyl)
-ϖ-methoxypoly(oxyethylen)-40
sodium salt, fully hydrogenated
soy phosphatidylcholine,
cholesterol, ammonium
sulphate, sucrose, histidine,
water for injections,
hydrochloric acid and sodium
hydroxide.

Keep out of the sight and
reach of children.

Store in a refrigerator.
Do not freeze.

Read the package leaflet
before use.

Baxter Healthcare Limited

Caxton Way,

Thetford,

Norfolk,

IP24 3SE,

United Kingdom

PLGB 00116/0255